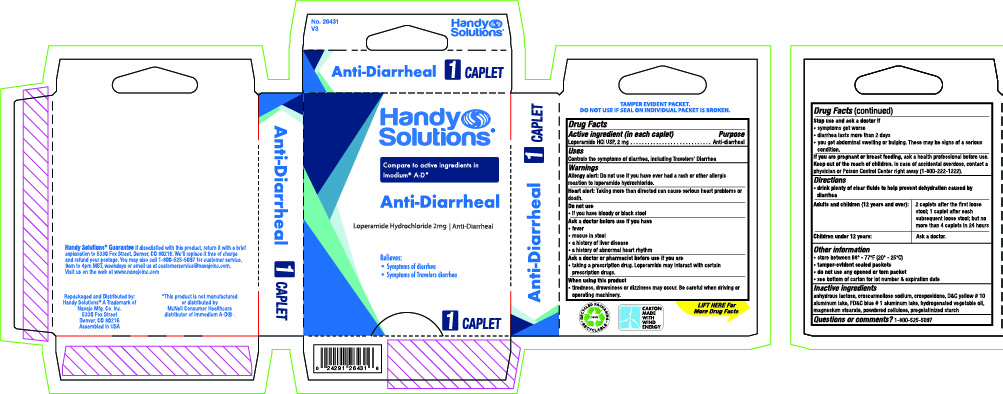 DRUG LABEL: Handy Solutions Anti-Diarrheal
NDC: 67751-162 | Form: TABLET
Manufacturer: Navajo Manufacturing Company Inc.
Category: otc | Type: HUMAN OTC DRUG LABEL
Date: 20230315

ACTIVE INGREDIENTS: LOPERAMIDE HYDROCHLORIDE 2 mg/1 1
INACTIVE INGREDIENTS: ANHYDROUS LACTOSE; CROSCARMELLOSE SODIUM; CROSPOVIDONE; D&C YELLOW NO. 10; FD&C BLUE NO. 1; MAGNESIUM STEARATE; POWDERED CELLULOSE

Handy Solutions Anti-Diarrheal

Active ingredient (in each caplet)

Loperamide Hydrochloride 2 mg

Purpose

Antidiarrheal

Uses

Controls the symptoms of diarrhea, including Traveler’s diarrhea

Warnings

Allergy alert: Do not use if you have ever had a rash or other allergic reaction to Loperamide HCl.

Do not use

• if you have bloody or black stools

Ask a doctor before use if you have

• a fever
• mucus in stool
• a history of liver disease

Ask a doctor or pharmacist before use if you are

• taking antibiotics

When using this product

• tiredness, drowsiness or dizziness may occur
• be careful when driving or operating machinery

Stop use and ask a doctor if

• symptoms get worse
• diarrhea lasts more than 2 days
• you get abdominal swelling or bulging. These may be signs of a serious condition.

If you are pregnant or breast feeding,

ask a health professional before use.

Keep this and all drugs out of the reach of children.

In case of accidental overdose, contact a physician or Poison Control Center right away.

Directions

do not use more than directed
drink plenty of clear fluids to help prevent dehydration caused by diarrhea

Adults and children (12 years and older): | Take 2 caplets after the first loose bowel movement followed by 1 caplet after each subsequent loose bowel movement but no more than 4 caplets in 24 hours.
Children under 12 years: | Do not give to children under 12 years of age.

Other information

• store between 68º - 77ºF (20º - 25ºC)
• tamper-evident sealed packets
• do not use any opened or torn packet

Inactive ingredients

anhydrous lactose, croscarmellose sodium, crospovidone, D&C yellow # 10, FD&C blue # 1, hydrogenated vegetable oil, magnesium stearate, powdered cellulose, pregelatinized starch

Questions or comments?

1-800-525-5097